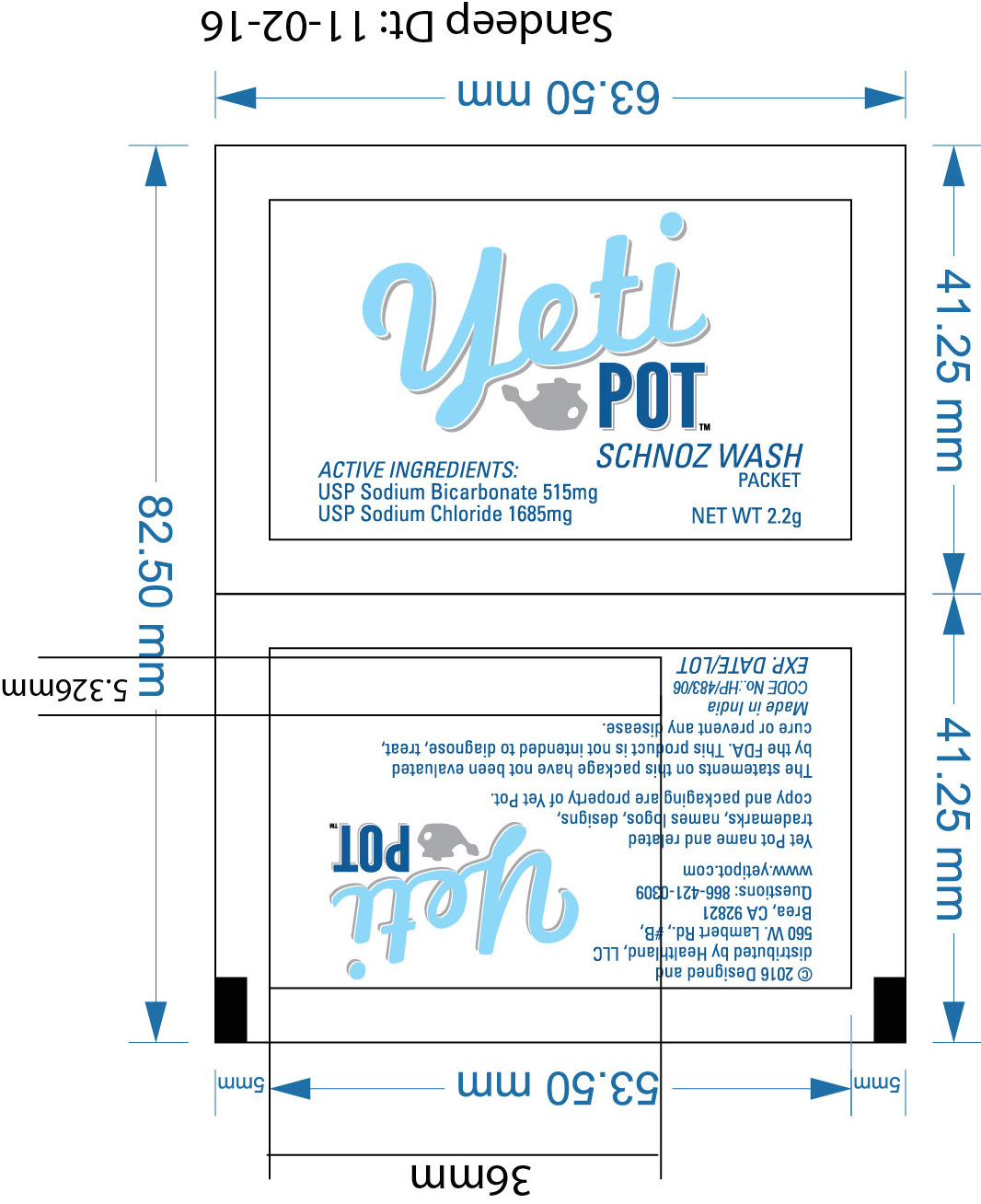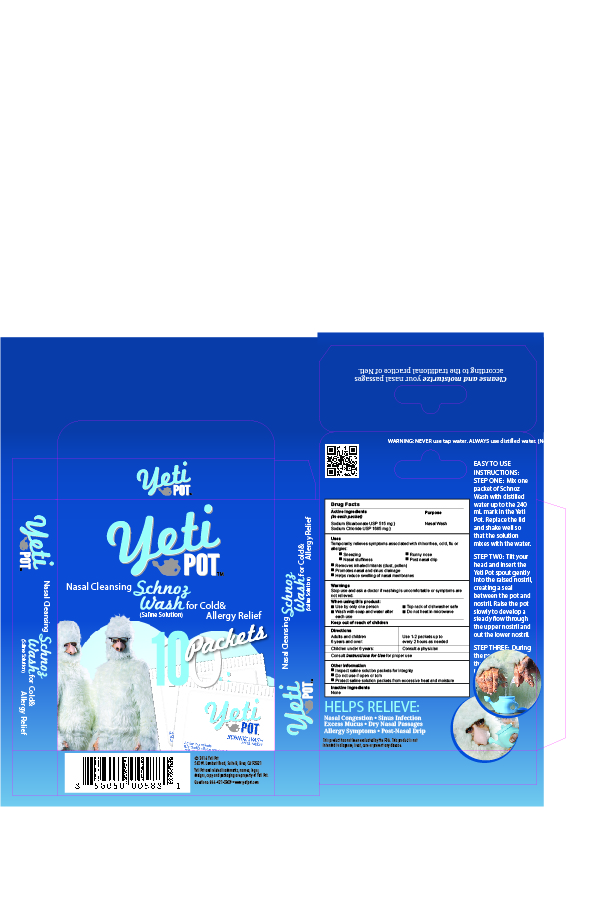 DRUG LABEL: YETI POT- SCHNOZ WASH
NDC: 70708-786 | Form: GRANULE, FOR SOLUTION
Manufacturer: HEALTHLAND LLC
Category: otc | Type: HUMAN OTC DRUG LABEL
Date: 20160507

ACTIVE INGREDIENTS: SODIUM BICARBONATE 515 mg/1 mg; SODIUM CHLORIDE 1685 mg/1 mg
INACTIVE INGREDIENTS: WATER 240 mg/1 mg

Warnings

Stop use and ask doctor if washing is uncomfortable or symptoms are not relieved.

When using this product

Use by only one person

Wash with soap and water after each use

Top rack of dishwasher safe

Do not heat in microwave

Keep out of reach of children

Other Information

-Inspect saline solution packets for integrity

-Do not use if open or torn

-Protect saline solution packets from excessive heat andmoisture

Uses

-Temporarily relieves systoms associated with rhinorrhea,cold,flu or allergies:

-Sneezing Runny nose Nasal stuffiness Post Nasal drip

-Removes inhaled irritants(dust, pollen)

-Promotesnasal and sinus drainage

-Help reduce swelling of nasal membranes

Drug Facts

Active Ingredients Purpose

(in each Packet)

Sodium Bicarbonate USP 515 mg Nasal Wash

Sodium Chloride USP 1685 mg

Directions

Adults and children 6 years and over : Use 1-2 packets every 2 hours as needed

Children under 6 years : Consult a physician

EASY TO USE INSTRUCTIONS

STEP ONE: Mix one packet of Schnoz Wash with distilled water up to the 240 ml mark in the Yeti Pot. Replace the lid and shake well so that the solution mixes witht he water.

STEP TWO : Tilt your head and insert the Yeti Pot spout gently into the raised nostril, creating a seal between the pot and nostril.Raise the pot slowly to develop a steady flow through the upper nostril and out the lower nostril.

STEP THREE: During the process breathe through your mouth. Upon completion , exhale firmly several times to clear the nasal passages.Reverse the tilt of your head and repeat the other process on the other side.

Inactive Ingredient

None